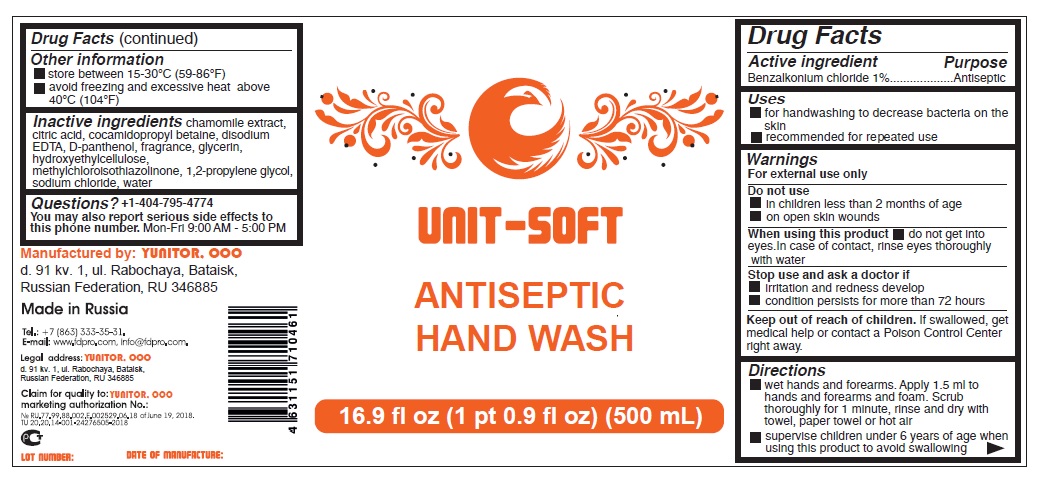 DRUG LABEL: UNIT - SOFT antiseptic hand wash
NDC: 80407-101 | Form: LIQUID
Manufacturer: YUNITOR, OOO
Category: otc | Type: HUMAN OTC DRUG LABEL
Date: 20200915

ACTIVE INGREDIENTS: BENZALKONIUM CHLORIDE 10 mg/1 mL
INACTIVE INGREDIENTS: CHAMOMILE; CITRIC ACID MONOHYDRATE; COCAMIDOPROPYL BETAINE; EDETATE DISODIUM ANHYDROUS; DEXPANTHENOL; GLYCERIN; HYDROXYETHYL CELLULOSE, UNSPECIFIED; METHYLCHLOROISOTHIAZOLINONE; PROPYLENE GLYCOL; SODIUM CHLORIDE; WATER

UNIT - SOFT ANTISEPTIC HAND WASH

Active ingredient

Benzalkonium chloride 1%

Purpose

Antiseptic

Uses

■ for handwashing to decrease bacteria on the skin

■ recommended for repeated use

Warnings

For external use only

Do not use

■ in children less than 2 months of age

■ on open skin wounds

When using this product ■ do not get into eyes.In case of contact, rinse eyes thoroughly with water

Stop use and ask a doctor if

■ irritation and redness develop

■ condition persists for more than 72 hours

Keep out of reach of children. If swallowed, get medical help or contact a Poison Control Center right away.

Directions

■ wet hands and forearms. Apply 1.5 ml to hands and forearms and foam. Scrub thoroughly for 1 minute, rinse and dry with towel, paper towel or hot air

■ supervise children under 6 years of age when using this product to avoid swallowing

Other information

■ store between 15-30°C (59-86°F)

■ avoid freezing and excessive heat above 40°C (104°F)

INACTIVE INGREDIENT

Inactive ingredients chamomile extract, citric acid, cocamidopropyl betaine, disodium EDTA, D-panthenol, fragrance, glycerin,

hydroxyethylcellulose, methylchloroisothiazolinone, 1,2-propylene glycol, sodium chloride, water

Questions? +1-404-795-4774

You may also report serious side effects to this phone number. Mon-Fri 9:00 AM - 5:00 PM

Manufactured by: YUNITOR, OOO

d. 91 kv. 1, ul. Rabochaya, Bataisk,

Russian Federation, RU 346885

Made in Russia

Tel.: +7 (863) 333-35-31.

Email: www.fdpro.com, info@fdpro.com

Legal address: YUNITOR, OOO

d. 91 kv. 1, ul. Rabochaya, Bataisk,

Russian Federation, RU 346885

Claim for quality to: YUNITOR, OOO